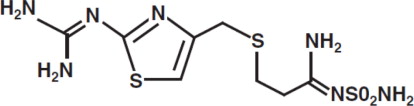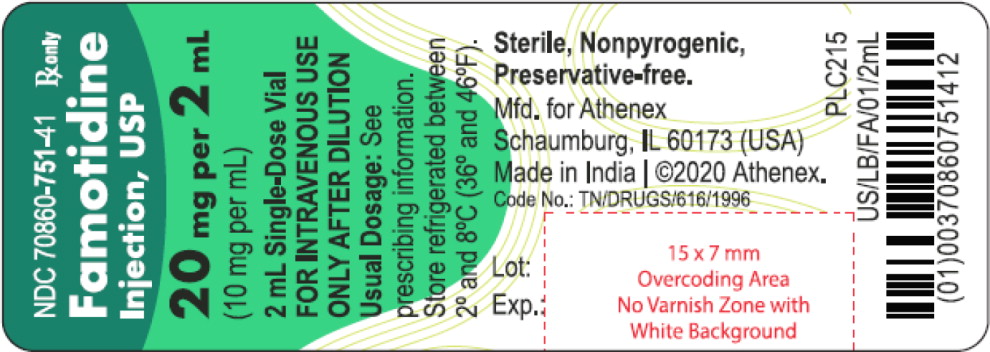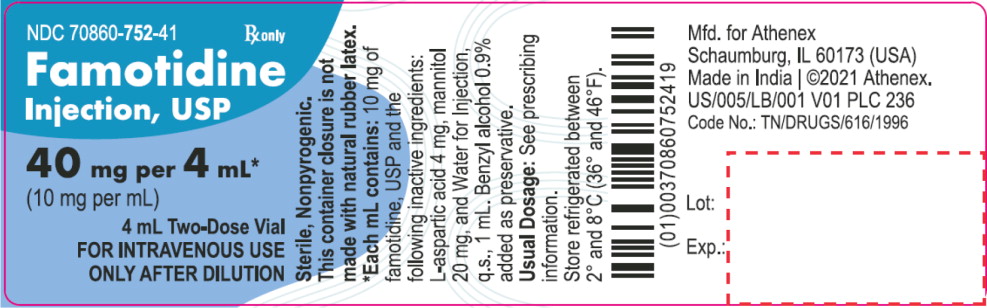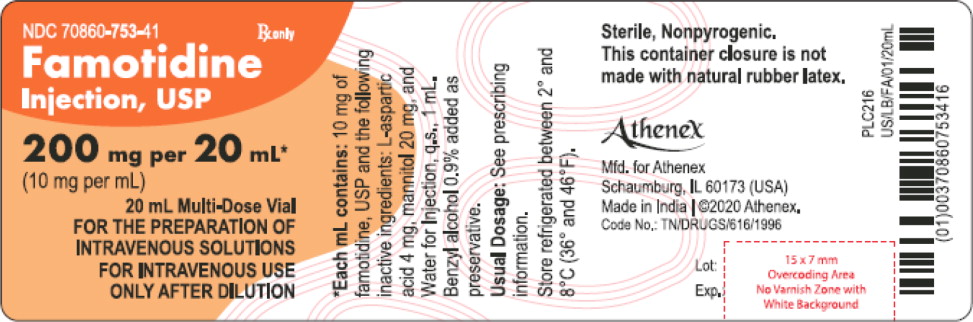 DRUG LABEL: Famotidine
NDC: 70860-751 | Form: INJECTION, SOLUTION
Manufacturer: Athenex Pharmaceutical Division, LLC.
Category: prescription | Type: HUMAN PRESCRIPTION DRUG LABEL
Date: 20250128

ACTIVE INGREDIENTS: FAMOTIDINE 10 mg/1 mL
INACTIVE INGREDIENTS: ASPARTIC ACID; MANNITOL; WATER

Famotidine Injection, USP

Athenex
Rx only

DESCRIPTION

The active ingredient in Famotidine Injection, USP is a histamine H2-receptor antagonist. Famotidine is [1-Amino-3-[[[2-[(diaminomethylene)amino]-4-thiazolyl]methyl]thio] propylidene] sulfamide. Its structural formula is:

C8H15N7O2S3

MW 337.45

Famotidine is a white to pale yellow crystalline compound that is freely soluble in glacial acetic acid, slightly soluble in methanol, very slightly soluble in water, and practically insoluble in ethanol.

Famotidine Injection is supplied as a sterile concentrated solution for intravenous injection. Each mL of the single-dose solution contains 10 mg of famotidine and the following inactive ingredients: L-aspartic acid 4 mg, mannitol 20 mg, and Water for Injection q.s. 1 mL. The multi-dose solution also contains benzyl alcohol 0.9% added as preservative.

CLINICAL PHARMACOLOGY IN ADULTS

GI Effects

Famotidine is a competitive inhibitor of histamine H2-receptors. The primary clinically important pharmacologic activity of famotidine is inhibition of gastric secretion. Both the acid concentration and volume of gastric secretion are suppressed by famotidine, while changes in pepsin secretion are proportional to volume output.

In normal volunteers and hypersecretors, famotidine inhibited basal and nocturnal gastric secretion, as well as secretion stimulated by food and pentagastrin. After oral administration, the onset of the antisecretory effect occurred within one hour; the maximum effect was dose-dependent, occurring within one to three hours. Duration of inhibition of secretion by doses of 20 and 40 mg was 10 to 12 hours.

After intravenous administration, the maximum effect was achieved within 30 minutes. Single intravenous doses of 10 and 20 mg inhibited nocturnal secretion for a period of 10 to 12 hours. The 20 mg dose was associated with the longest duration of action in most subjects.

Single evening oral doses of 20 and 40 mg inhibited basal and nocturnal acid secretion in all subjects; mean nocturnal gastric acid secretion was inhibited by 86% and 94%, respectively, for a period of at least 10 hours. The same doses given in the morning suppressed food-stimulated acid secretion in all subjects. The mean suppression was 76% and 84%, respectively, 3 to 5 hours after administration, and 25% and 30%, respectively, 8 to 10 hours after administration. In some subjects who received the 20 mg dose, however, the antisecretory effect was dissipated within 6 to 8 hours. There was no cumulative effect with repeated doses. The nocturnal intragastric pH was raised by evening doses of 20 and 40 mg of famotidine to mean values of 5.0 and 6.4, respectively. When famotidine was given after breakfast, the basal daytime interdigestive pH at 3 and 8 hours after 20 or 40 mg of famotidine was raised to about 5.

Famotidine had little or no effect on fasting or postprandial serum gastrin levels. Gastric emptying and exocrine pancreatic function were not affected by famotidine.

Other Effects

Systemic effects of famotidine in the CNS, cardiovascular, respiratory or endocrine systems were not noted in clinical pharmacology studies. Also, no antiandrogenic effects were noted (see ADVERSE REACTIONS). Serum hormone levels, including prolactin, cortisol, thyroxine (T4), and testosterone, were not altered after treatment with famotidine.

Pharmacokinetics

Orally administered famotidine is incompletely absorbed, and its bioavailability is 40 to 45%. Famotidine undergoes minimal first-pass metabolism. After oral doses, peak plasma levels occur in 1 to 3 hours. Plasma levels after multiple doses are similar to those after single doses. Fifteen to 20% of famotidine in plasma is protein bound. Famotidine has an elimination half-life of 2.5 to 3.5 hours. Famotidine is eliminated by renal (65 to 70%) and metabolic (30 to 35%) routes. Renal clearance is 250 to 450 mL/min, indicating some tubular excretion. Twenty-five to 30% of an oral dose and 65 to 70% of an intravenous dose are recovered in the urine as unchanged compound. The only metabolite identified in man is the S-oxide.

There is a close relationship between creatinine clearance values and the elimination half-life of famotidine. In patients with severe renal insufficiency, i.e., creatinine clearance less than 10 mL/min, the elimination half-life of famotidine may exceed 20 hours and adjustment of dose or dosing intervals in moderate and severe renal insufficiency may be necessary (see PRECAUTIONS, DOSAGE AND ADMINISTRATION).

In elderly patients, there are no clinically significant age-related changes in the pharmacokinetics of famotidine.

However, in elderly patients with decreased renal function, the clearance of the drug may be decreased (see PRECAUTIONS, Geriatric Use).

Clinical Studies

The majority of clinical study experience involved oral administration of famotidine tablets, and is provided herein for reference.

Duodenal Ulcer

In a U.S. multicenter, double-blind study in outpatients with endoscopically confirmed duodenal ulcer, orally administered famotidine was compared to placebo. As shown in Table 1, 70% of patients treated with famotidine 40 mg h.s. were healed by week 4.

Table 1: Outpatients with Endoscopically Confirmed Healed Duodenal Ulcers
 | Famotidine 40 mg h.s. (N=89) | Famotidine 20 mg b.i.d. (N=84) | Placebo h.s. (N=97)
Week 2 | *32% | *38% | 17%
Week 4 | *70% | *67% | 31%
* Statistically significantly different than placebo (p<0.001)

Patients not healed by week 4 were continued in the study. By week 8, 83% of patients treated with famotidine had healed versus 45% of patients treated with placebo. The incidence of ulcer healing with famotidine was significantly higher than with placebo at each time point based on proportion of endoscopically confirmed healed ulcers.

In this study, time to relief of daytime and nocturnal pain was significantly shorter for patients receiving famotidine than for patients receiving placebo; patients receiving famotidine also took less antacid than the patients receiving placebo.

Long-Term Maintenance Treatment of Duodenal Ulcers

Famotidine, 20 mg p.o. h.s. was compared to placebo h.s. as maintenance therapy in two double-blind, multicenter studies of patients with endoscopically confirmed healed duodenal ulcers. In the U.S. study the observed ulcer incidence within 12 months in patients treated with placebo was 2.4 times greater than in the patients treated with famotidine. The 89 patients treated with famotidine had a cumulative observed ulcer incidence of 23.4% compared to an observed ulcer incidence of 56.6% in the 89 patients receiving placebo (p<0.01). These results were confirmed in an international study where the cumulative observed ulcer incidence within 12 months in the 307 patients treated with famotidine was 35.7%, compared to an incidence of 75.5% in the 325 patients treated with placebo (p<0.01).

Gastric Ulcer

In both a U.S. and an international multicenter, double-blind study in patients with endoscopically confirmed active benign gastric ulcer, orally administered famotidine, 40 mg h.s., was compared to placebo h.s. Antacids were permitted during the studies, but consumption was not significantly different between the famotidine and placebo groups. As shown in Table 2, the incidence of ulcer healing (dropouts counted as unhealed) with famotidine was statistically significantly better than placebo at weeks 6 and 8 in the U.S. study, and at weeks 4, 6 and 8 in the international study, based on the number of ulcers that healed, confirmed by endoscopy.

Table 2: Patients with Endoscopically Confirmed Healed Gastric Ulcers
 | U.S. Study |  | International Study
 | Famotidine 40 mg h.s. (N=74) | Placebo h.s. (N=75) | Famotidine 40 mg h.s. (N=149) | Placebo h.s. (N=145)
Week 4 | 45% | 39% | ***47% | 31%
Week 6 | ***66% | 44% | ***65% | 46%
Week 8 | **78% | 64% | ***80% | 54%
**,*** Statistically significantly better than placebo (p≤0.05, p≤0.01, respectively)

Time to complete relief of daytime and nighttime pain was statistically significantly shorter for patients receiving famotidine than for patients receiving placebo; however, in neither study was there a statistically significant difference in the proportion of patients whose pain was relieved by the end of the study (week 8).

Gastroesophageal Reflux Disease (GERD)

Orally administered famotidine was compared to placebo in a U.S. study that enrolled patients with symptoms of GERD and without endoscopic evidence of erosion or ulceration of the esophagus. Famotidine 20 mg b.i.d. was statistically significantly superior to 40 mg h.s. and to placebo in providing a successful symptomatic outcome, defined as moderate or excellent improvement of symptoms (Table 3).

Table 3: % Successful Symptomatic Outcome
 | Famotidine 20 mg b.i.d. (N=154) | Famotidine 40 mg h.s. (N=149) | Placebo (N=73)
Week 6 | 82† | 69 | 62
†p≤0.01 vs placebo

By two weeks of treatment, symptomatic success was observed in a greater percentage of patients taking famotidine 20 mg b.i.d. compared to placebo (p≤0.01).

Symptomatic improvement and healing of endoscopically verified erosion and ulceration were studied in two additional trials. Healing was defined as complete resolution of all erosions or ulcerations visible with endoscopy. The U.S. study comparing famotidine 40 mg p.o. b.i.d. to placebo and famotidine 20 mg p.o. b.i.d., showed a significantly greater percentage of healing for famotidine 40 mg b.i.d. at weeks 6 and 12 (Table 4).

Table 4: % Endoscopic Healing - U.S. Study
 | Famotidine 40 mg b.i.d. (N=127) | Famotidine 20 mg b.i.d. (N=125) | Placebo (N=66)
Week 6 | 48††,‡ | 32 | 18
Week 12 | 69††,††† | 54†† | 29
†† p≤0.01 vs placebo
†††p≤0.05 vs famotidine 20 mg b.i.d.
‡ p≤0.01 vs famotidine 20 mg b.i.d.

As compared to placebo, patients who received famotidine had faster relief of daytime and nighttime heartburn and a greater percentage of patients experienced complete relief of nighttime heartburn. These differences were statistically significant.

In the international study, when famotidine 40 mg p.o. b.i.d. was compared to ranitidine 150 mg p.o. b.i.d., a statistically significantly greater percentage of healing was observed with famotidine 40 mg b.i.d. at week 12 (Table 5). There was, however, no significant difference among treatments in symptom relief.

Table 5: % Endoscopic Healing - International Study
 | Famotidine 40 mg b.i.d. (N=175) | Famotidine 20 mg b.i.d. (N=93) | Ranitidine 150 mg b.i.d. (N=172)
Week 6 | 48 | 52 | 42
Week 12 | 71‡‡ | 68 | 60
‡‡p≤0.05 vs Ranitidine 150 mg b.i.d.

Pathological Hypersecretory Conditions (e.g., Zollinger-Ellison Syndrome, Multiple Endocrine Adenomas)

In studies of patients with pathological hypersecretory conditions such as Zollinger-Ellison Syndrome with or without multiple endocrine adenomas, famotidine significantly inhibited gastric acid secretion and controlled associated symptoms. Orally administered doses from 20 to 160 mg q 6 h maintained basal acid secretion below 10 mEq/hr; initial doses were titrated to the individual patient need and subsequent adjustments were necessary with time in some patients. Famotidine was well tolerated at these high dose levels for prolonged periods (greater than 12 months) in eight patients, and there were no cases reported of gynecomastia, increased prolactin levels, or impotence which were considered to be due to the drug.

CLINICAL PHARMACOLOGY IN PEDIATRIC PATIENTS

Pharmacokinetics

Table 6presents pharmacokinetic data from clinical trials and a published study in pediatric patients (<1 year of age; N=27) given famotidine IV 0.5 mg/kg and from published studies of small numbers of pediatric patients (1 to 15 years of age) given famotidine intravenously. Areas under the curve (AUCs) are normalized to a dose of 0.5 mg/kg IV for pediatric patients 1 to 15 years of age and compared with an extrapolated 40 mg intravenous dose in adults (extrapolation based on results obtained with a 20 mg IV adult dose).

Table 6: Pharmacokinetic Parametersaof Intravenous Famotidine
Age (N=number of patients) | Area Under the Curve (AUC) (ng-hr/mL) | Total Clearance (Cl) (L/hr/kg) | Volume of Distribution (Vd) (L/kg) | Elimination Half-Life (T1/2) (hours)
0 to 1 monthc (N=10) | NA | 0.13 ± 0.06 | 1.4 ± 0.4 | 10.5 ± 5.4
0 to 3 monthsd (N=6) | 2688 ± 847 | 0.21 ± 0.06 | 1.8 ± 0.3 | 8.1 ± 3.5
>3 to 12 monthsd (N=11) | 1160 ± 474 | 0.49 ± 0.17 | 2.3 ± 0.7 | 4.5 ± 1.1
1 to 11 yrs (N=20) | 1089 ± 834 | 0.54 ± 0.34 | 2.07 ± 1.49 | 3.38 ± 2.6
11 to 15 yrs (N=6) | 1140 ± 320 | 0.48 ± 0.14 | 1.5 ± 0.4 | 2.3 ± 0.4
Adult (N=16) | 1726b | 0.39 ± 0.14 | 1.3 ± 0.2 | 2.83 ± 0.99
aValues are presented as means ± SD unless indicated otherwise
bMean value only
cSingle center study
dMulticenter study

Plasma clearance is reduced and elimination half-life is prolonged in pediatric patients 0 to 3 months of age compared to older pediatric patients. The pharmacokinetic parameters for pediatric patients, ages >3 months to 15 years, are comparable to those obtained for adults.

Bioavailability studies of 8 pediatric patients (11 to 15 years of age) showed a mean oral bioavailability of 0.5 compared to adult values of 0.42 to 0.49. Oral doses of 0.5 mg/kg achieved AUCs of 645 ± 249 ng-hr/mL and 580 ± 60 ng-hr/mL in pediatric patients <1 year of age (N=5) and in pediatric patients 11 to 15 years of age, respectively, compared to 482 ± 181 ng-hr/mL in adults treated with 40 mg orally.

Pharmacodynamics

Pharmacodynamics of famotidine were evaluated in 5 pediatric patients 2 to 13 years of age using the sigmoid Emaxmodel. These data suggest that the relationship between serum concentration of famotidine and gastric acid suppression is similar to that observed in one study of adults (Table 7).

Table 7: Pharmacodynamics of Famotidine Using the Sigmoid EmaxModel
 | EC50(ng/mL)*
Pediatric Patients | 26 ± 13
Data from one study
a) Healthy adult subjects | 26.5 ± 10.3
b) Adult patients with upper GI bleeding | 18.7 ± 10.8
* Serum concentration of famotidine associated with 50% maximum gastric acid reduction. Values are presented as means ± SD

Five published studies (Table 8) examined the effect of famotidine on gastric pH and duration of acid suppression in pediatric patients. While each study had a different design, acid suppression data over time are summarized as follows:

Table 8
Dosage | Route | Effecta | Number of Patients (age range)
0.5 mg/kg, single-dose | IV | gastric pH >4 for 19.5 hours (17.3, 21.8)c | 11 (5 to 19 days)
0.3 mg/kg, single-dose | IV | gastric pH >3.5 for 8.7 ± 4.7bhours | 6 (2 to 7 years)
0.4 to 0.8 mg/kg | IV | gastric pH >4 for 6 to 9 hours | 18 (2 to 69 months)
0.5 mg/kg, single-dose | IV | a >2 pH unit increase above baseline in gastric pH for >8 hours | 9 (2 to 13 years)
0.5 mg/kg b.i.d. | IV | gastric pH >5 for 13.5 ± 1.8bhours | 4 (6 to 15 years)
0.5 mg/kg b.i.d. | Oral | gastric pH >5 for 5 ± 1.1bhours | 4 (11 to 15 years)
aValues reported in published literature
bMeans ± SD
cMean (95% confidence interval)

The duration of effect of famotidine IV 0.5 mg/kg on gastric pH and acid suppression was shown in one study to be longer in pediatric patients <1 month of age than in older pediatric patients. This longer duration of gastric acid suppression is consistent with the decreased clearance in pediatric patients <3 months of age (see Table 6).

INDICATIONS AND USAGE

Famotidine Injection, supplied as a concentrated solution for intravenous injection, is intended for intravenous use only. Famotidine Injection is indicated in some hospitalized patients with pathological hypersecretory conditions or intractable ulcers, or as an alternative to the oral dosage forms for short term use in patients who are unable to take oral medication for the following conditions:

1. Short term treatment of active duodenal ulcer.Most adult patients heal within 4 weeks; there is rarely reason to use famotidine at full dosage for longer than 6 to 8 weeks. Studies have not assessed the safety of famotidine in uncomplicated active duodenal ulcer for periods of more than eight weeks.
2. Maintenance therapy for duodenal ulcer patients at reduced dosage after healing of an active ulcer.Controlled studies in adults have not extended beyond one year.
3. Short term treatment of active benign gastric ulcer.Most adult patients heal within 6 weeks. Studies have not assessed the safety or efficacy of famotidine in uncomplicated active benign gastric ulcer for periods of more than 8 weeks.
4. Short term treatment of gastroesophageal reflux disease (GERD).Famotidine is indicated for short term treatment of patients with symptoms of GERD (see CLINICAL PHARMACOLOGY IN ADULTS, Clinical Studies). Famotidine is also indicated for the short term treatment of esophagitis due to GERD including erosive or ulcerative disease diagnosed by endoscopy (see CLINICAL PHARMACOLOGY IN ADULTS, Clinical Studies).
5. Treatment of pathological hypersecretory conditions (e.g., Zollinger-Ellison Syndrome, multiple endocrine adenomas)(see CLINICAL PHARMACOLOGY IN ADULTS, Clinical Studies).

CONTRAINDICATIONS

Hypersensitivity to any component of these products. Cross sensitivity in this class of compounds has been observed. Therefore, Famotidine Injection should not be administered to patients with a history of hypersensitivity to other H2-receptor antagonists.

WARNINGS

Famotidine Injection 4 mL and 20 mL multiple dose vials contain the preservative benzyl alcohol. There have been reports of fatal ‘gasping syndrome’ in neonates (children less than one month of age) following the administration of intravenous solutions containing the preservative benzyl alcohol. Symptoms include a striking onset of gasping respiration, hypotension, bradycardia, and cardiovascular collapse. Benzyl alcohol, given its small size, presumably crosses the placental barrier into immature fetal tissues as readily as it crosses the blood-brain barrier. Therefore, Famotidine Injection from multiple dose vials containing benzyl alcohol should not be used in neonates and pregnant women.

PRECAUTIONS

General

Symptomatic response to therapy with famotidine does not preclude the presence of gastric malignancy.

Patients with Moderate or Severe Renal Insufficiency

Since CNS adverse effects have been reported in patients with moderate and severe renal insufficiency, longer intervals between doses or lower doses may need to be used in patients with moderate (creatinine clearance <50 mL/min) or severe (creatinine clearance <10 mL/min) renal insufficiency to adjust for the longer elimination half-life of famotidine (see CLINICAL PHARMACOLOGY IN ADULTS, DOSAGE AND ADMINISTRATION).

Drug Interactions

No drug interactions have been identified. Studies with famotidine in man, in animal models, and in vitrohave shown no significant interference with the disposition of compounds metabolized by the hepatic microsomal enzymes, e.g., cytochrome P450 system. Compounds tested in man include warfarin, theophylline, phenytoin, diazepam, aminopyrine and antipyrine. Indocyanine green as an index of hepatic drug extraction has been tested and no significant effects have been found.

Carcinogenesis, Mutagenesis, Impairment of Fertility

In a 106 week study in rats and a 92 week study in mice given oral doses of up to 2000 mg/kg/day (approximately 2500 times the recommended human dose for active duodenal ulcer), there was no evidence of carcinogenic potential for famotidine.

Famotidine was negative in the microbial mutagen test (Ames test) using Salmonella typhimuriumand Escherichia coliwith or without rat liver enzyme activation at concentrations up to 10,000 mcg/plate. In in vivostudies in mice, with a micronucleus test and a chromosomal aberration test, no evidence of a mutagenic effect was observed.

In studies with rats given oral doses of up to 2000 mg/kg/day or intravenous doses of up to 200 mg/kg/day, fertility and reproductive performance were not affected.

Pregnancy

Reproductive studies have been performed in rats and rabbits at oral doses of up to 2000 and 500 mg/kg/day, respectively, and in both species at IV doses of up to 200 mg/kg/day, and have revealed no significant evidence of impaired fertility or harm to the fetus due to famotidine. While no direct fetotoxic effects have been observed, sporadic abortions occurring only in mothers displaying marked decreased food intake were seen in some rabbits at oral doses of 200 mg/kg/day (250 times the usual human dose) or higher. There are, however, no adequate or well-controlled studies in pregnant women. Because animal reproductive studies are not always predictive of human response, this drug should be used during pregnancy only if clearly needed.

Nursing Mothers

Studies performed in lactating rats have shown that famotidine is secreted into breast milk. Transient growth depression was observed in young rats suckling from mothers treated with maternotoxic doses of at least 600 times the usual human dose. Famotidine is detectable in human milk. Because of the potential for serious adverse reactions in nursing infants from famotidine, a decision should be made whether to discontinue nursing or discontinue the drug, taking into account the importance of the drug to the mother.

Pediatric Patients <1 Year of Age

Use of famotidine in pediatric patients <1 year of age is supported by evidence from adequate and well-controlled studies of famotidine in adults, and by the following studies in pediatric patients <1 year of age.

Two pharmacokinetic studies in pediatric patients <1 year of age (N=48) demonstrated that clearance of famotidine in patients >3 months to 1 year of age is similar to that seen in older pediatric patients (1 to 15 years of age) and adults. In contrast, pediatric patients 0 to 3 months of age had famotidine clearance values that were 2- to 4-fold less than those in older pediatric patients and adults. These studies also show that the mean bioavailability in pediatric patients <1 year of age after oral dosing is similar to older pediatric patients and adults. Pharmacodynamic data in pediatric patients 0 to 3 months of age suggest that the duration of acid suppression is longer compared with older pediatric patients, consistent with the longer famotidine half-life in pediatric patients 0 to 3 months of age (see CLINICAL PHARMACOLOGY IN PEDIATRIC PATIENTS, Pharmacokineticsand Pharmacodynamics).

In a double-blinded, randomized, treatment-withdrawal study, 35 pediatric patients <1 year of age who were diagnosed as having gastroesophageal reflux disease were treated for up to 4 weeks with famotidine oral suspension (0.5 mg/kg/dose or 1 mg/kg/dose). Although an intravenous famotidine formulation was available, no patients were treated with intravenous famotidine in this study. Also, caregivers were instructed to provide conservative treatment including thickened feedings. Enrolled patients were diagnosed primarily by history of vomiting (spitting up) and irritability (fussiness). The famotidine dosing regimen was once daily for patients <3 months of age and twice daily for patients ≥3 months of age. After 4 weeks of treatment, patients were randomly withdrawn from the treatment and followed an additional 4 weeks for adverse events and symptomatology. Patients were evaluated for vomiting (spitting up), irritability (fussiness) and global assessments of improvement. The study patients ranged in age at entry from 1.3 to 10.5 months (mean 5.6 ± 2.9 months), 57% were female, 91% were white and 6% were black. Most patients (27/35) continued into the treatment withdrawal phase of the study. Two patients discontinued famotidine due to adverse events. Most patients improved during the initial treatment phase of the study. Results of the treatment withdrawal phase were difficult to interpret because of small numbers of patients. Of the 35 patients enrolled in the study, agitation was observed in 5 patients on famotidine that resolved when the medication was discontinued; agitation was not observed in patients on placebo (see ADVERSE REACTIONS, Pediatric Patients).

These studies suggest that a starting dose of 0.5 mg/kg/dose of famotidine oral suspension may be of benefit for the treatment of GERD for up to 4 weeks once daily in patients <3 months of age and twice daily in patients 3 months to <1 year of age; the safety and benefit of famotidine treatment beyond 4 weeks have not been established. Famotidine should be considered for the treatment of GERD only if conservative measures (e.g., thickened feedings) are used concurrently and if the potential benefit outweighs the risk.

Pediatric Patients 1 to 16 Years of Age

Use of famotidine in pediatric patients 1 to 16 years of age is supported by evidence from adequate and well-controlled studies of famotidine in adults and by the following studies in pediatric patients: In published studies in small numbers of pediatric patients 1 to 15 years of age, clearance of famotidine was similar to that seen in adults. In pediatric patients 11 to 15 years of age, oral doses of 0.5 mg/kg were associated with a mean area under the curve (AUC) similar to that seen in adults treated orally with 40 mg. Similarly, in pediatric patients 1 to 15 years of age, intravenous doses of 0.5 mg/kg were associated with a mean AUC similar to that seen in adults treated intravenously with 40 mg. Limited published studies also suggest that the relationship between serum concentration and acid suppression is similar in pediatric patients 1 to 15 years of age as compared with adults. These studies suggest that the starting dose for pediatric patients 1 to 16 years of age is 0.25 mg/kg intravenously (injected over a period of not less than two minutes or as a 15-minute infusion) q 12 h up to 40 mg/day.

While published uncontrolled clinical studies suggest effectiveness of famotidine in the treatment of peptic ulcer, data in pediatric patients are insufficient to establish percent response with dose and duration of therapy. Therefore, treatment duration (initially based on adult duration recommendations) and dose should be individualized based on clinical response and/or gastric pH determination and endoscopy. Published uncontrolled studies in pediatric patients have demonstrated gastric acid suppression with doses up to 0.5 mg/kg intravenously q 12 h.

Geriatric Use

Of the 4,966 subjects in clinical studies who were treated with famotidine, 488 subjects (9.8%) were 65 and older, and 88 subjects (1.7%) were greater than 75 years of age. No overall differences in safety or effectiveness were observed between these subjects and younger subjects. However, greater sensitivity of some older patients cannot be ruled out.

No dosage adjustment is required based on age (see CLINICAL PHARMACOLOGY IN ADULTS, Pharmacokinetics). This drug is known to be substantially excreted by the kidney, and the risk of toxic reactions to this drug may be greater in patients with impaired renal function. Because elderly patients are more likely to have decreased renal function, care should be taken in dose selection, and it may be useful to monitor renal function. Dosage adjustment in the case of moderate or severe renal impairment is necessary (see PRECAUTIONS, Patients with Moderate or Severe Renal Insufficiencyand DOSAGE AND ADMINISTRATION, Dosage Adjustment for Patients with Moderate or Severe Renal Insufficiency).

ADVERSE REACTIONS

The adverse reactions listed below have been reported during domestic and international clinical trials in approximately 2500 patients. In those controlled clinical trials in which famotidine tablets were compared to placebo, the incidence of adverse experiences in the group which received famotidine tablets, 40 mg at bedtime, was similar to that in the placebo group.

The following adverse reactions have been reported to occur in more than 1% of patients on therapy with famotidine in controlled clinical trials, and may be causally related to the drug: headache (4.7%), dizziness (1.3%), constipation (1.2%) and diarrhea (1.7%).

The following other adverse reactions have been reported infrequently in clinical trials or since the drug was marketed. The relationship to therapy with famotidine has been unclear in many cases. Within each category the adverse reactions are listed in order of decreasing severity.

Body as a Whole:fever, asthenia, fatigue

Cardiovascular:arrhythmia, AV block, palpitation, prolonged QT interval

Gastrointestinal:cholestatic jaundice, hepatitis, elevated liver enzyme, vomiting, nausea, abdominal discomfort, anorexia, dry mouth

Hematologic:agranulocytosis, pancytopenia, leukopenia, thrombocytopenia

Hypersensitivity:anaphylaxis, angioedema, orbital or facial edema, urticaria, rash, conjunctival injection, bronchospasm

Musculoskeletal:rhabdomyolysis, musculoskeletal pain, muscle cramps, arthralgia

Nervous System/Psychiatric:seizure, hallucinations, confusion, agitation, depression, anxiety, decreased libido, paresthesia, insomnia, somnolence

Respiratory:interstitial pneumonia

Skin:toxic epidermal necrolysis/Stevens Johnson syndrome, pruritus, dry skin, flushing

Special Senses:tinnitus, taste disorder

Other:impotence

The adverse reactions reported for Famotidine Tablets may also occur with Famotidine for Oral Suspension or Famotidine Injection. In addition, transient irritation at the injection site has been observed with Famotidine Injection.

Pediatric Patients

In a clinical study in 35 pediatric patients <1 year of age with GERD symptoms [e.g. vomiting (spitting up), irritability (fussing)], agitation was observed in 5 patients on famotidine that resolved when the medication was discontinued.

To report SUSPECTED ADVERSE REACTIONS, contact Athenex Pharmaceutical Division, LLC. at 1-855-273-0154 or FDA at 1-800-FDA-1088 orwww.fda.gov/medwatch.

OVERDOSAGE

The adverse reactions in overdose cases are similar to the adverse reactions encountered in normal clinical experience (see ADVERSE REACTIONS). Oral doses of up to 640 mg/day have been given to adult patients with pathological hypersecretory conditions with no serious adverse effects. In the event of overdosage, treatment should be symptomatic and supportive. Unabsorbed material should be removed from the gastrointestinal tract, the patient should be monitored, and supportive therapy should be employed.

The intravenous LD50of famotidine for mice and rats ranged from 254 to 563 mg/kg and the minimum lethal single IV dose in dogs was approximately 300 mg/kg. Signs of acute intoxication in IV treated dogs were emesis, restlessness, pallor of mucous membranes or redness of mouth and ears, hypotension, tachycardia and collapse. The oral LD50of famotidine in male and female rats and mice was greater than 3000 mg/kg and the minimum lethal acute oral dose in dogs exceeded 2000 mg/kg. Famotidine did not produce overt effects at high oral doses in mice, rats, cats and dogs, but induced significant anorexia and growth depression in rabbits starting with 200 mg/kg/day orally.

DOSAGE AND ADMINISTRATION

In some hospitalized patients with pathological hypersecretory conditions or intractable ulcers, or in patients who are unable to take oral medication, Famotidine Injection may be administered until oral therapy can be instituted.

The recommended dosage for Famotidine Injection in adult patients is 20 mg intravenously q 12 h.

The doses and regimen for parenteral administration in patients with GERD have not been established.

Dosage for Pediatric Patients <1 Year of Age Gastroesophageal Reflux Disease (GERD)

See PRECAUTIONS, Pediatric Patients <1 Year of Age.

The studies described in PRECAUTIONS, Pediatric Patients <1 Year of Agesuggest the following starting doses in pediatric patients <1 year of age: Gastroesophageal Reflux Disease (GERD) - 0.5 mg/kg/dose of famotidine oral suspension for the treatment of GERD for up to 8 weeks once daily in patients <3 months of age and 0.5 mg/kg/dose twice daily in patients 3 months to <1 year of age. Patients should also be receiving conservative measures (e.g., thickened feedings). The use of intravenous famotidine in pediatric patients <1 year of age with GERD has not been adequately studied.

Dosage for Pediatric Patients 1 to 16 Years of Age

See PRECAUTIONS, Pediatric Patients 1 to 16 Years of Age.

The studies described in PRECAUTIONS, Pediatric Patients 1 to 16 Years of Agesuggest that the starting dose in pediatric patients 1 to 16 years of age is 0.25 mg/kg intravenously (injected over a period of not less than two minutes or as a 15-minute infusion) q 12 h up to 40 mg/day.

While published uncontrolled clinical studies suggest effectiveness of famotidine in the treatment of peptic ulcer, data in pediatric patients are insufficient to establish percent response with dose and duration of therapy. Therefore, treatment duration (initially based on adult duration recommendations) and dose should be individualized based on clinical response and/or gastric pH determination and endoscopy. Published uncontrolled studies in pediatric patients 1 to 16 years of age have demonstrated gastric acid suppression with doses up to 0.5 mg/kg intravenously q 12 h.

Dosage Adjustments for Patients with Moderate or Severe Renal Insufficiency

In adult patients with moderate (creatinine clearance <50 mL/min) or severe (creatinine clearance <10 mL/min) renal insufficiency, the elimination half-life of famotidine is increased. For patients with severe renal insufficiency, it may exceed 20 hours, reaching approximately 24 hours in anuric patients. Since CNS adverse effects have been reported in patients with moderate and severe renal insufficiency, to avoid excess accumulation of the drug in patients with moderate or severe renal insufficiency, the dose of Famotidine Injection may be reduced to half the dose, or the dosing interval may be prolonged to 36 to 48 hours as indicated by the patient's clinical response.

Based on the comparison of pharmacokinetic parameters for famotidine in adults and pediatric patients, dosage adjustment in pediatric patients with moderate or severe renal insufficiency should be considered.

Pathological Hypersecretory Conditions (e.g., Zollinger-Ellison Syndrome, Multiple Endocrine Adenomas)

The dosage of famotidine in patients with pathological hypersecretory conditions varies with the individual patient. The recommended adult intravenous dose is 20 mg q 12 h. Doses should be adjusted to individual patient needs and should continue as long as clinically indicated. In some patients, a higher starting dose may be required. Oral doses up to 160 mg q 6 h have been administered to some adult patients with severe Zollinger-Ellison Syndrome.

To prepare intravenous solutions,aseptically dilute 2 mL of Famotidine Injection (solution containing 10 mg/mL) with Sodium Chloride Injection 0.9% or other compatible intravenous solution (see Stability) to a total volume of either 5 mL or 10 mL and inject over a period of not less than 2 minutes.

To prepare intravenous infusion solutions,aseptically dilute 2 mL of Famotidine Injection with 100 mL of Dextrose 5% or other compatible solution (see Stability), and infuse over a 15 to 30 minute period.

Concomitant Use of Antacids

Antacids may be given orally concomitantly if needed.

Stability

Parenteral drug products should be inspected visually for particulate matter and discoloration prior to administration whenever solution and container permit.

When added to or diluted with most commonly used intravenous solutions, e.g., Water for Injection, Sodium Chloride Injection 0.9%, Dextrose Injection 5% and 10% or Lactated Ringer's Injection, diluted Famotidine Injection is physically and chemically stable (i.e., maintains at least 90% of initial potency) for 7 days at room temperature — see HOW SUPPLIED, Storage Conditions.

When added to or diluted with Sodium Bicarbonate Injection 5%, Famotidine Injection at a concentration of 0.2 mg/mL (the recommended concentration of famotidine intravenous infusion solutions) is physically and chemically stable (i.e., maintains at least 90% of initial potency) for 7 days at room temperature — see HOW SUPPLIED, Storage Conditions. However, a precipitate may form at higher concentrations of Famotidine Injection (>0.2 mg/mL) in Sodium Bicarbonate Injection 5%.

HOW SUPPLIED

FOR INTRAVENOUS USE ONLY

Famotidine Injection, USP, is supplied as follows:

 | Famotidine Injection, USP (Preservative-free)
NDC | (10 mg per mL) | Package Factor
70860-751-02 | 20 mg per 2 mL Single-Dose Vial | 25 vials per carton
 | Famotidine Injection, USP (Preservative)
NDC | (10 mg per mL) | Package Factor
70860-752-04 | 40 mg per 4 mL Two-Dose Vial | 10 vials per carton
70860-753-20 | 200 mg per 20 mL Multi-Dose Vial | 10 vials per carton

Storage Conditions

Store Famotidine Injection refrigerated between 2° and 8°C (36° and 46°F).If solution freezes, bring to room temperature; allow sufficient time to solubilize all the components.

Although diluted Famotidine Injection has been shown to be physically and chemically stable for 7 days at room temperature, there are no data on the maintenance of sterility after dilution. Therefore, it is recommended that if not used immediately after preparation, diluted solutions of Famotidine Injection should be refrigerated and used within 48 hours (see DOSAGE AND ADMINISTRATION).

Sterile, Nonpyrogenic.
The container closure is not made with natural rubber latex.

Athenex
Mfd. for Athenex
Schaumburg, IL 60173 (USA)
Made in India
©2020 Athenex

July 2020

PACKAGE LABEL – PRINCIPAL DISPLAY PANEL – Vial Label

NDC 70860-751-41

Famotidine Injection, USP

20 mg per 2 mL

(10 mg per mL)

Rx only

2 mL Single-Dose Vial

FOR INTRAVENOUS USE ONLY AFTER DILUTION

PACKAGE LABEL – PRINCIPAL DISPLAY PANEL – Vial Label

NDC 70860-752-41

Famotidine Injection, USP

40 mg per 4 mL

(10 mg per mL)

Rx only

4 mL Two-Dose Vial

FOR INTRAVENOUS USE ONLY AFTER DILUTION

PACKAGE LABEL – PRINCIPAL DISPLAY PANEL – Vial Label

NDC 70860-753-41

Famotidine Injection, USP

200 mg per 20 mL

(10 mg per mL)

Rx only

20 mL Multi-Dose Vial

FOR THE PREPARATION OF INTRAVENOUS SOLUTIONS

FOR INTRAVENOUS USE ONLY AFTER DILUTION